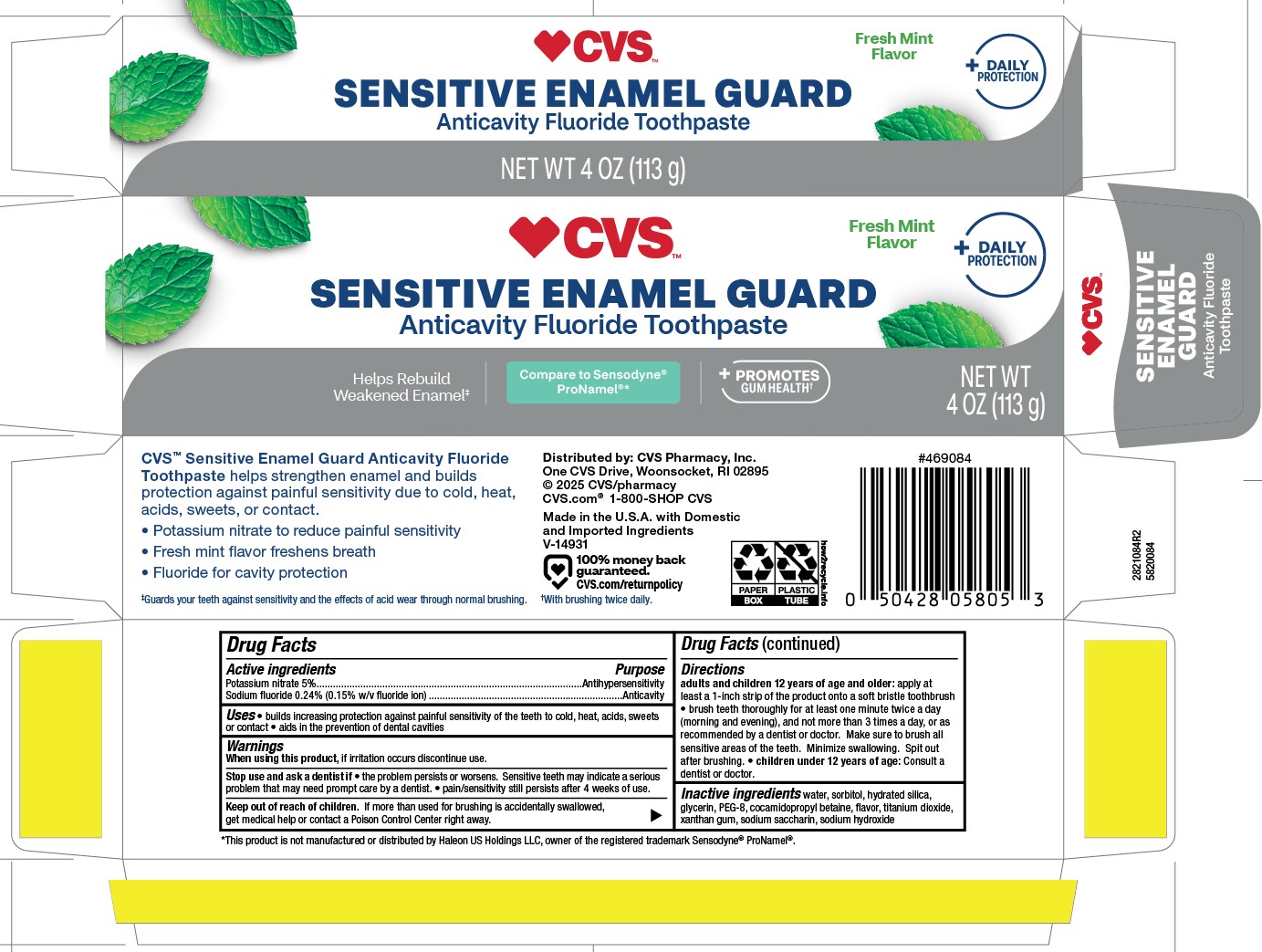 DRUG LABEL: CVS
NDC: 51316-128 | Form: PASTE, DENTIFRICE
Manufacturer: CVS Pharmacy
Category: otc | Type: HUMAN OTC DRUG LABEL
Date: 20251121

ACTIVE INGREDIENTS: SODIUM FLUORIDE 0.15 g/100 g; POTASSIUM NITRATE 5 g/100 g
INACTIVE INGREDIENTS: WATER; SACCHARIN SODIUM; SORBITOL; POLYETHYLENE GLYCOL 400; TITANIUM DIOXIDE; SODIUM HYDROXIDE; GLYCERIN; XANTHAN GUM; HYDRATED SILICA; COCAMIDOPROPYL BETAINE

5820084 CVS Sensitive Enamel Guard Mint

Active ingredients / Purpose

Potassium nitrate 5%....................................................Antihypersensitivity

Sodium fluoride 0..24% (0.15% w/v fluoride ion).........................Anticavity

Uses

- builds increasing protection against painful sensitivty of teeth to cold, heat, acids, sweets or contact
- aids in the prevention of dental cavities

When using this product, if irritation accurs discontinue use.

Keep out of reach of children. If more than used for brushing is accidentally swallowed, get medical help or contact a Poison Control Center right away.

Stop use and ask a dentist if

- if the problem worsens. Sensitive teeth may indicate a serious problem that may need prompt care by a dentist.
- pain/sensitivity still persists after 4 weeks of use.

Directions

Brush teeth thoroughly for at least one minute, preferably after each meal or at least twice a day (morning and evening) or as recommended by a dentist or physican. Make sure to brush all sensitive areas of the teeth. Minimize swallowing. Spit out after brushing.

DOSAGE AND ADMINISTRATION

adults and children 12 years of age and older: apply at least a 1-inch strip of the product onto a soft bristle toothbrush.

- brush thoroughly for at least one minute twice a day, or as recommended by a dentist or doctor.
- Children under 12 years of age: Consult a dentist or a doctor.

Other Information

Store in a cool dry place. Keep tube capped when not in use.

Inactive ingredients

water, sorbitol, hydrated silica, glycerin, PEG-8, cocamidopropyl betaine, flavor, titanium dioxide, xanthan gum, sodium saccharin, sodium hydroxide